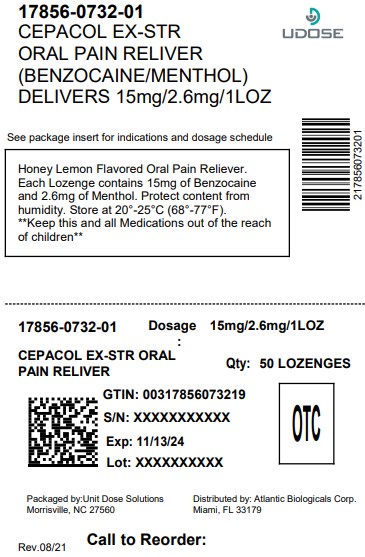 DRUG LABEL: Cepacol 

NDC: 17856-0732 | Form: LOZENGE
Manufacturer: ATLANTIC BIOLOGICALS CORP.
Category: otc | Type: HUMAN OTC DRUG LABEL
Date: 20250624

ACTIVE INGREDIENTS: BENZOCAINE 15 mg/1 1; MENTHOL 2.6 mg/1 1
INACTIVE INGREDIENTS: D&C YELLOW NO. 10; FD&C YELLOW NO. 6; ISOMALT; MALTITOL; PROPYLENE GLYCOL; WATER; SODIUM BICARBONATE; SUCRALOSE

Cēpacol®
Extra Strength* Sore Throat honey lemon

Drug Facts

ACTIVE INGREDIENT

PURPOSE

Active ingredients (in each lozenge) | Purposes
Benzocaine 15 mg | Oral pain reliever
Menthol 2.6 mg | Oral pain reliever

Uses

Temporary relief of occasional

- sore throat
- sore mouth
- minor mouth irritation
- pain associated with canker sores

Warnings

METHEMOGLOBINEMIA WARNING

Use of this product may cause methemoglobinemia, a rare but serious condition that must be treated promptly because it reduces the amount of oxygen carried in blood. Stop use and seek immediate medical attention if you or a child in your care develops:

- pale, gray, or blue colored skin (cyanosis)
- headache
- rapid heart rate
- shortness of breath
- dizziness or lightheadedness
- fatigue or lack of energy

Allergy alert

- Do not use this product if you have a history of allergy to local anesthetics such as procaine, butacaine, benzocaine, or any other 'caine' anesthetics.

Sore throat warning

- If sore throat is severe, persists for more than 2 days, is accompanied or followed by fever, headache, rash, nausea, or vomiting, consult a doctor promptly.

Stop use and ask a doctor or dentist if

- sore mouth symptoms do not improve in 7 days
- irritation, pain, or redness persists or worsens
- swelling, rash, or fever develops

PREGNANCY OR BREAST FEEDING

If pregnant or breast-feeding,ask a health professional before use.

KEEP OUT OF REACH OF CHILDREN

Keep this and all drugs out of the reach of children.In case of overdose, get medical help or contact a Poison Control Center right away.

Do not exceed recommended dosage.

Directions

- adults and children 5 years of age and older: allow one lozenge to dissolve slowly in the mouth; may be repeated every 2 hours as needed or as directed by a doctor or dentist.
- children under 5 years of age: do not use

Other information

- store between 20-25°C (68-77°F)
- protect contents from humidity

Inactive ingredients

D&C yellow no. 10, FD&C yellow no. 6, flavors, isomalt, maltitol, propylene glycol, purified water, sodium bicarbonate, sucralose

Questions?

Call 1-866-682-4639

You may also report side effects to this phone number.

Dist. by: Reckitt Benckiser
Parsippany, NJ 07054-0224
Made in England